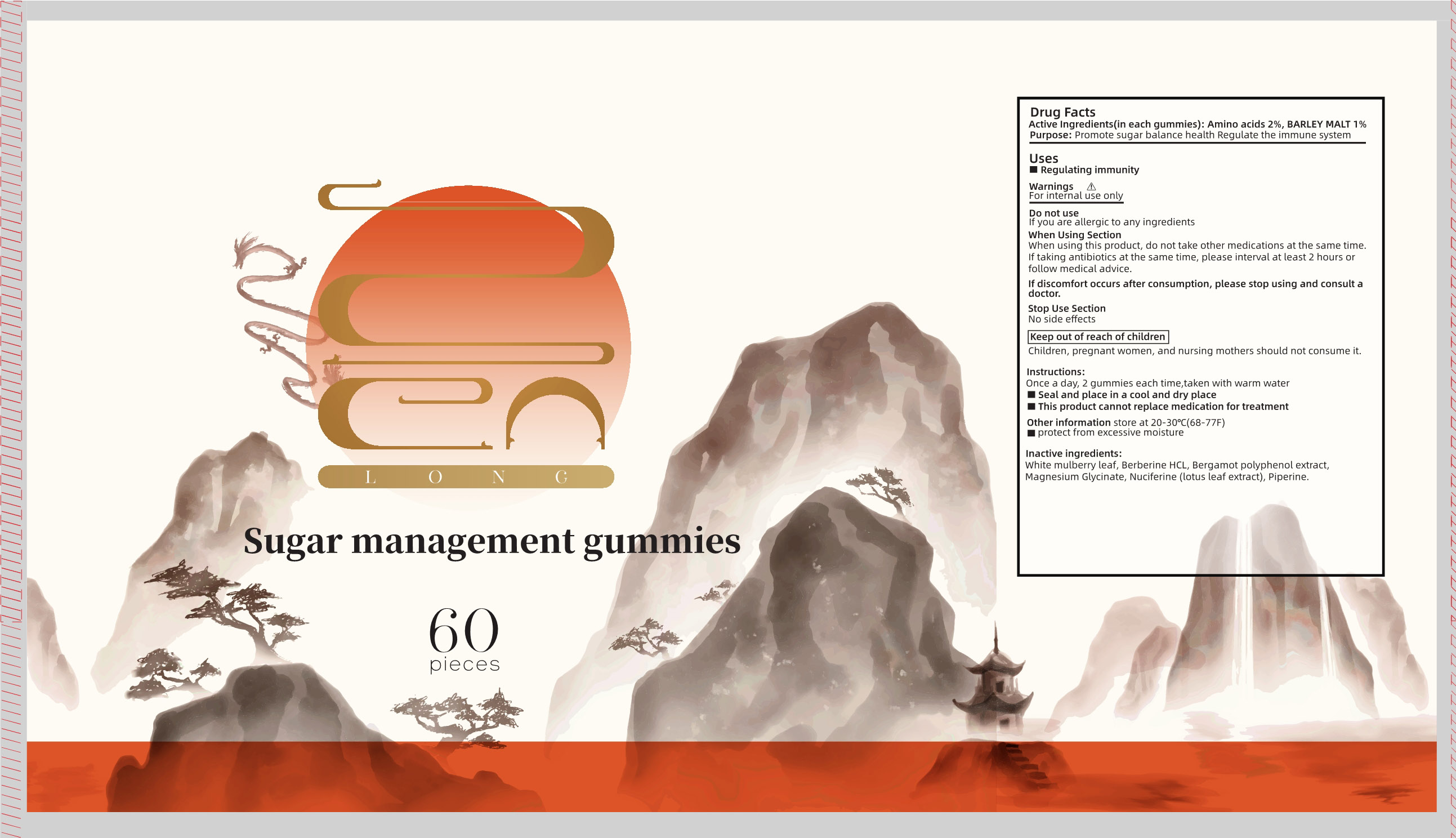 DRUG LABEL: sugar management gummies
NDC: 83739-005 | Form: CHEWABLE GEL
Manufacturer: XIAN CHIANG COMPANY LIMITED
Category: otc | Type: HUMAN OTC DRUG LABEL
Date: 20250216

ACTIVE INGREDIENTS: AMINO ACIDS 2 g/100 1; BARLEY MALT 1 g/100 1
INACTIVE INGREDIENTS: BERGAMOT OIL; BERBERINE; MORUS ALBA LEAF; NUCIFERINE; PIPERINE; MAGNESIUM GLYCINATE

83739-005

ACTIVE INGREDIENT

Amino acids 2%, BARLEY MALT 1%

Purpose

Promote sugar balance health Regulate the immune syst

Uses

Regulating immunity

Warnings

For internal use only

Do not use

If you are allergic to any ingredients

When Using Section

When using this product , do not take other medications at the same time, If taking antibiotics at the same time , please interval at least 2 hours orfollow medical advice

If discomfort occurs after consumption , please stop using and consult a doctor

Stop Use Section

No side effects

Instructions

Once a day , 2 gummies each time , taken with warm wate

Seal and place in a cool and dry place

This product cannot replace medication for treatment

Keep out of reach of children

Children , pregnant women , and nursing mothers should not consume it

Other information

Other information store at 20-30°C (68-77F)

protect from excessive moisture

Inactive ingredients

White mulberry leaf , Berberine HCL , Bergamot polyphenol extract ,Magnesium Glycinate , Nuciferine (lotus leaf extract) , Piperine